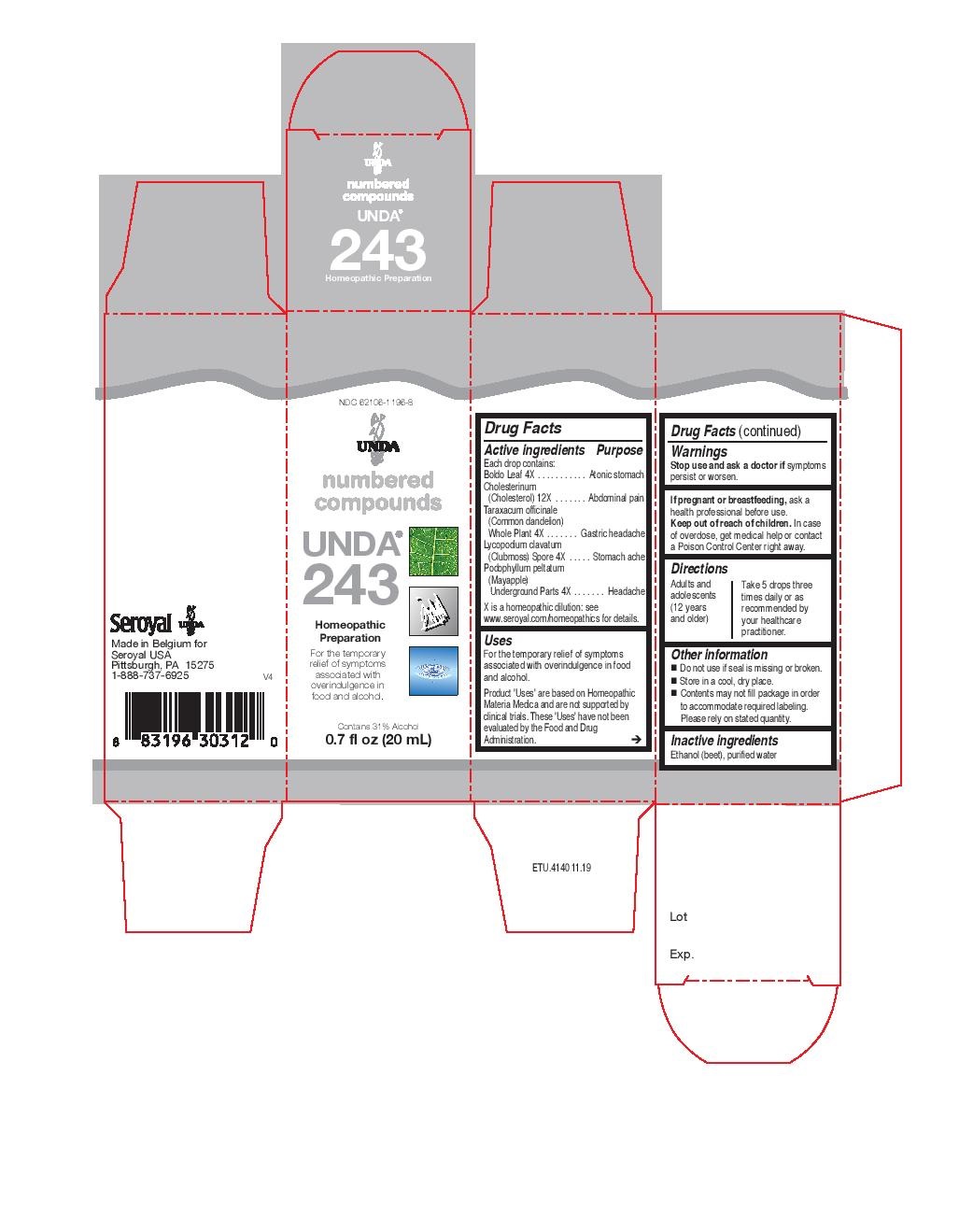 DRUG LABEL: UNDA 243
NDC: 62106-1196 | Form: LIQUID
Manufacturer: Seroyal USA
Category: homeopathic | Type: HUMAN OTC DRUG LABEL
Date: 20221109

ACTIVE INGREDIENTS: TARAXACUM OFFICINALE 4 [hp_X]/20 mL; LYCOPODIUM CLAVATUM SPORE 4 [hp_X]/20 mL; PODOPHYLLUM 4 [hp_X]/20 mL; PEUMUS BOLDUS LEAF 4 [hp_X]/20 mL; CHOLESTEROL 12 [hp_X]/20 mL
INACTIVE INGREDIENTS: ALCOHOL; WATER

UNDA 243

Active ingredients
Each drop contains:
Boldo Leaf 4X
Cholesterinum (Cholesterol) 12X
Taraxacum officinale (Common dandelion) Whole Plant 4X
Lycopodium clavatum (Clubmoss) Spore 4X
Podophyllum peltatum (Mayapple) Underground Parts 4X

Uses
For the temporary relief of symptoms associated with overindulgence in food and alcohol.

Warnings
Stop use and ask a doctor if symptoms persist or worsen.

If pregnant or breastfeeding, ask a health professional before use.
Keep out of reach of children. In case of overdose, get medical help or contact
a Poison Control Center right away.

Keep out of reach of children.

PREGNANCY OR BREAST FEEDING

If pregnant or breastfeeding, ask a health professional before use.

Directions
Adults and adolescents (12 years and older)
Take 5 drops three times daily or as recommended by your healthcare practitioner.

Uses
For the temporary relief of symptoms associated with overindulgence in food and alcohol.

Directions
Adults and adolescents (12 years and older)
Take 5 drops three times daily or as recommended by your healthcare practitioner.

Inactive ingredients
Ethanol (beet), purified water

Other information
Do not use if seal is missing or broken.
Store in a cool, dry place.
Contents may not fill package in order to accommodate required labeling. Please rely on stated quantity.

PACKAGE LABEL

NDC 62106-1196-8

UNDA

numbered compounds

UNDA 243

Homeopathic Preparation

For the temporary relief of symptoms

associated with overindulgence in
food and alcohol.

Contains 31% Alcohol

0.7 fl oz (20 mL)